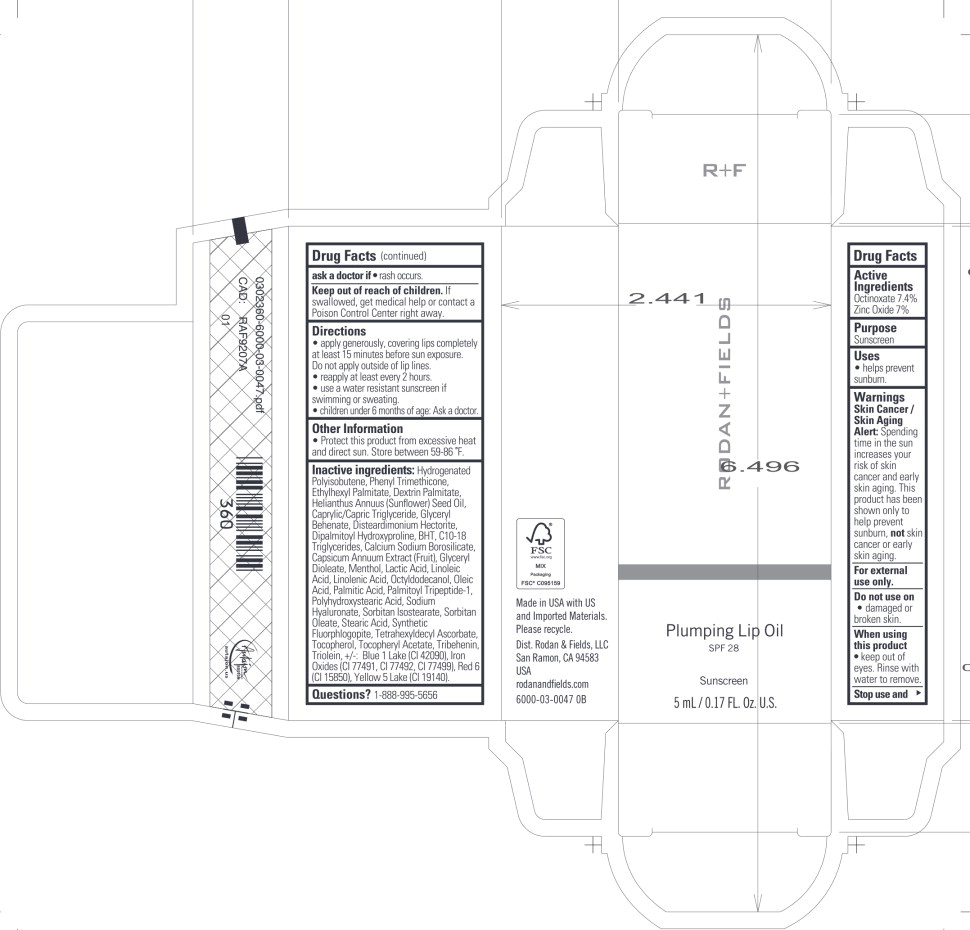 DRUG LABEL: Rodan and Fields Plumping Lip SPF 28 Sunscreen
NDC: 14222-3000 | Form: OIL
Manufacturer: Rodan & Fields
Category: otc | Type: HUMAN OTC DRUG LABEL
Date: 20241115

ACTIVE INGREDIENTS: Octinoxate 7.4 g/100 mL; Zinc Oxide 7 g/100 mL
INACTIVE INGREDIENTS: Hydrogenated Polyisobutene (1300 MW); Phenyl Trimethicone; Ethylhexyl Palmitate; Dextrin Palmitate (Corn; 20000 MW); Sunflower Oil; Medium-Chain Triglycerides; Glyceryl Monobehenate; Disteardimonium Hectorite; Dipalmitoyl Hydroxyproline; Butylated Hydroxytoluene; C10-18 Triglycerides; Calcium Sodium Borosilicate; Glyceryl Dioleate; Menthol; Lactic Acid; Linoleic Acid; Linolenic Acid; Octyldodecanol; Oleic Acid; Palmitic Acid; Palmitoyl Tripeptide-1; Hyaluronate Sodium; Sorbitan Isostearate; Sorbitan Monooleate; Stearic Acid; Magnesium Potassium Aluminosilicate Fluoride; Tetrahexyldecyl Ascorbate; Tocopherol; .Alpha.-Tocopherol Acetate; Tribehenin; Glyceryl Trioleate; FD&C Blue No. 1 Aluminum Lake; Ferric Oxide Red; D&C Red No. 6; FD&C YELLOW NO. 5; Polyhydroxystearic Acid (2300 MW); Capsicum

Drug Facts

Active Ingredients

Octinoxate 7.4%

Zinc Oxide 7%

Purpose

Sunscreen

Uses

- helps prevent sunburn.

Warnings Skin Cancer/ Skin Aging Alert:

Spending time in the sun increases your risk of skin cancer and early skin aging. This product has been shown only to help prevent sunburn, not skin cancer or early skin aging.

For external use only.

Do not use on

- damaged or broken skin.

When using this product

- keep out of eyes. Rinse with water to remove.

Stop use and ask a doctor if

- rash occurs.

Keep out of reach of children. If swallowed, get medical help or contact a Poison Control Center right away.

Directions

- apply generously, covering lips completely at least 15 minutes before sun exposure.

Do not apply outside of lip lines.

- reapply at least every 2 hours.
- use a water resistant sunscreen if swimming or sweating.
- children under 6 months of age: Ask a doctor.

Other Information

- Protect this product from excessive heat and direct sun. Store between 59-86°F.

Inactive ingredients:

Hydrogenated Polyisobutene, Phenyl Trimethicone, Ethylhexyl Palmitate, Dextrin Palmitate, Helianthus Annuus (Sunflower) Seed Oil, Caprylic/Capric Triglyceride, Glyceryl Behenate, Disteardimonium Hectorite, Dipalmitoyl Hydroxyproline, BHT, C10-18 Triglycerides, Calcium Sodium Borosilicate, Capsicum Annuum Extract (Fruit), Glyceryl Dioleate, Menthol, Lactic Acid, Linoleic Acid, Linolenic Acid, Octyldodecanol, Oleic Acid, Palmitic Acid, Palmitoyl Tripeptide-1, Polyhydroxystearic Acid, Sodium Hyaluronate, Sorbitan Isostearate, Sorbitan Oleate, Stearic Acid, Synthetic Fluorphlogopite, Tetrahexyldecyl Ascorbate, Tocopherol, Tocopheryl Acetate, Tribehenin, Triolein,+/-: Blue 1 Lake (Cl 42090), Iron Oxides (Cl 77491, Cl 77492, Cl 77499), Red 6 (Cl 15850), Yellow 5 Lake (Cl 19140).

Questions?

1-888-995-5656

Principal Display Panel – 5 mL Carton Label

RODAN + FIELDS

Plumping Lip Oil

SPF 28

Sunscreen

5 mL/0.17 FL. Oz. U.S.